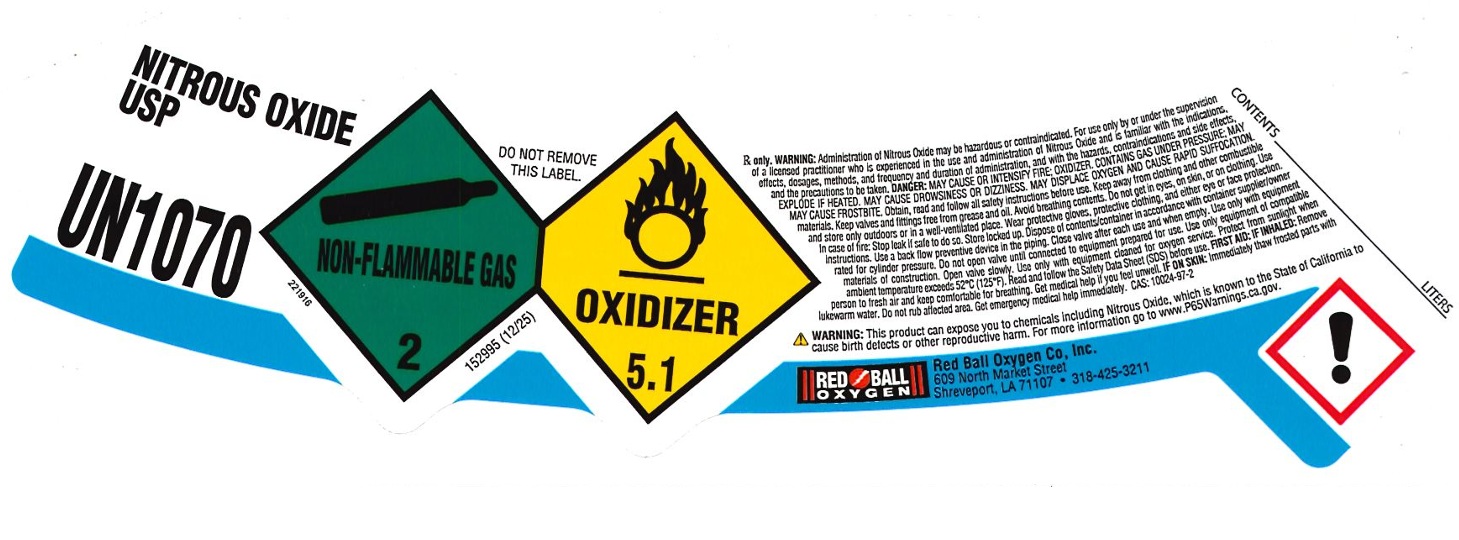 DRUG LABEL: Nitrous Oxide
NDC: 46362-003 | Form: GAS
Manufacturer: Red Ball Oxygen Co., Inc.
Category: prescription | Type: HUMAN PRESCRIPTION DRUG LABEL
Date: 20260206

ACTIVE INGREDIENTS: NITROUS OXIDE 992 mL/1 L

Nitrous Oxide

PACKAGE LABEL

NITROUS OXIDE USP

UN1070

DO NOT REMOVE THIS LABEL.

Rx only. WARNING: Administration of Nitrous Oxide may be hazardous or contraindicated. For use only by or under the supervision of a licensed practitioner who is experienced in the use and administration of Nitrous Oxide and is familiar with the indications, effects, dosages, methods, and frequency and duration of administration, and with the hazards, contraindications and side effects, and the precautions to be taken. DANGER: MAY CAUSE OR INTENSIFY FIRE; OXIDIZER. CONTAINS GAS UNDER PRESSURE; MAY EXPLODE IF HEATED. MAY CAUSE DROWSINESS OR DIZZINESS. MAY DISPLACE OXYGEN AND CAUSE RAPID SUFFOCATION. MAY CAUSE FROSTBITE. Obtain, read and follow all safety instructions before use. Keep away from clothing and other combustible materials. Keep valves and fittings free from grease and oil. Avoid breathing contents. Do not get in eyes, on skin, or on clothing. Use and store only outdoors or in a well-ventilated place. Wear protective gloves, protective clothing, and either eye or face protection. In case of fire: Stop leak if safe to do so. Store locked up. Dispose of contents/container in accordance with container supplier/owner instructions. Use a back flow preventive device in the piping. Close valve after each use and when empty. Use only with equipment rated for cylinder pressure. Do not open valve until connected to equipment cleaned for oxygen service. Protect from sunlight when ambient temperature exceeds 52 C (125 F). Read and follow the Safety Data Sheet (SDS) before use. FIRST AID: IF INHALED: Remove person to fresh air and keep comfortable for breathing. Get medical help if you feel unwell. IF ON SKIN: Immediately thaw frosted parts with lukewarm water. Do not rub affected area. Get emergency medical help immediately. CAS: 10024-97-2

WARNING: This product can expose you to chemicals including Nitrous Oxide, which is known to the State of California to cause birth defects or other reproductive harm. For more information go to www.P65Warnings.ca.gov.

RED BALL OXYGEN

Red Ball Oxygen Co, Inc.

609 North Market Street

Shreveport, LA 71107 318-425-3211

CONTENTS LITERS